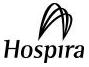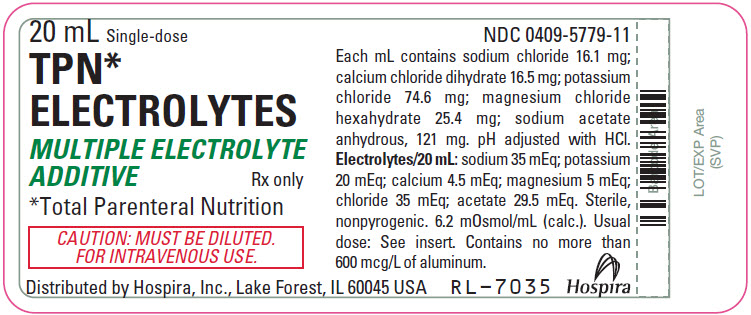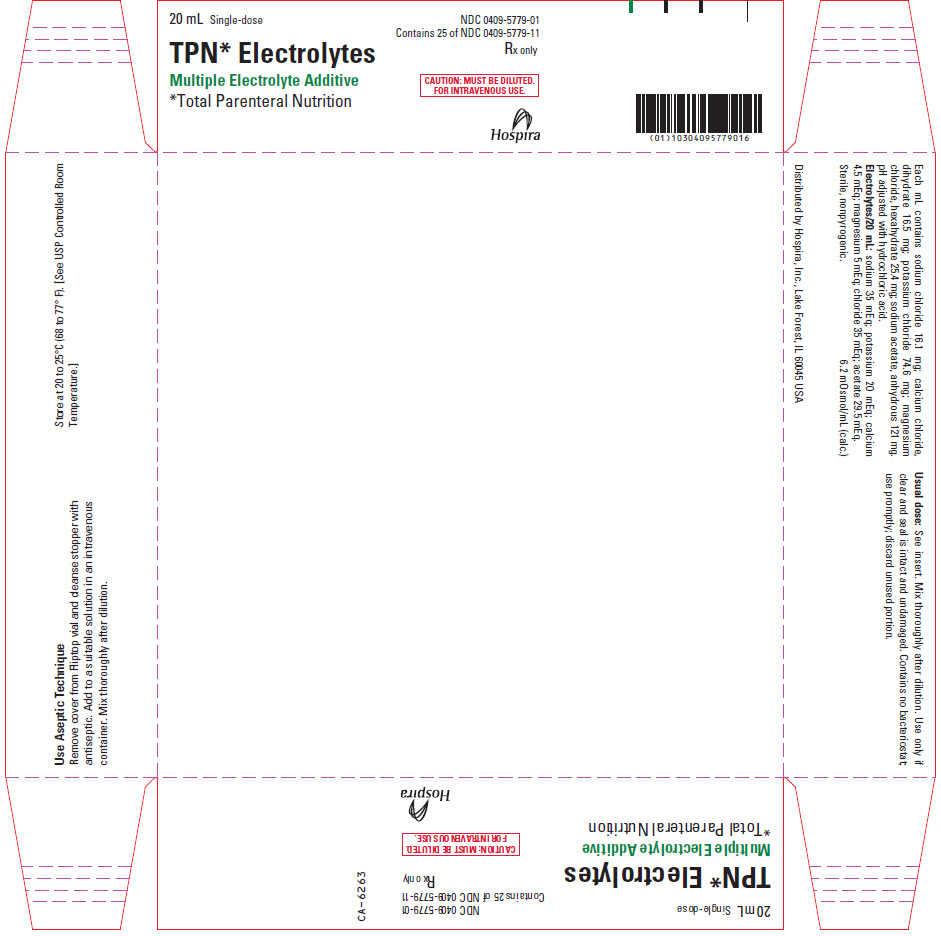 DRUG LABEL: TPN Electrolytes
NDC: 0409-5779 | Form: INJECTION, SOLUTION, CONCENTRATE
Manufacturer: Hospira, Inc.
Category: prescription | Type: HUMAN PRESCRIPTION DRUG LABEL
Date: 20241128

ACTIVE INGREDIENTS: SODIUM CHLORIDE 321 mg/20 mL; CALCIUM CHLORIDE 331 mg/20 mL; POTASSIUM CHLORIDE 1491 mg/20 mL; MAGNESIUM CHLORIDE 508 mg/20 mL; SODIUM ACETATE ANHYDROUS 2420 mg/20 mL
INACTIVE INGREDIENTS: WATER; HYDROCHLORIC ACID

TPN*
Electrolytes

Multiple Electrolyte Additive

Contains No Phosphate

Rx only

Concentrated Solution — For intravenous use only after dilution and thorough mixing.

Formulated to provide additive electrolytes for patients receiving total parenteral nutrition.

Plastic Vial

DESCRIPTION

TPN Electrolytes (multiple electrolyte additive) is a sterile, nonpyrogenic, concentrated solution of intra- and extracellular ions for intravenous infusion after dilution as a maintenance electrolyte replenisher only. It contains no phosphate and no bacteriostat, antimicrobial agent or added buffer. The pH is 6.6 (6.0 to 7.5). May contain hydrochloric acid for pH adjustment. The osmolar concentration is 6.2 mOsmol/mL (calc.).

__________________________

*Total Parenteral Nutrition

Ingredients and ion constituents of the solution are as follows:

Ingredient or Ion | mg/20 mL | mEq/20 mL
Sodium Chloride | 321
Calcium Chloride (dihydrate) | 331
Potassium Chloride | 1491
Magnesium Chloride (hexahydrate) | 508
Sodium Acetate (anhydrous) | 2420
Sodium (Na^+) |  | 35
Potassium (K^+) |  | 20
Calcium (Ca^++) |  | 4.5
Magnesium (Mg^++) |  | 5
Chloride (Cl^−) |  | 35
Acetate (CH3COO^−) |  | 29.5

Sodium Chloride, USP is chemically designated NaCl, a white crystalline compound freely soluble in water.

Calcium Chloride, USP dihydrate is chemically designated CaCl2 • 2H2O, white, odorless fragments or granules, freely soluble in water.

Potassium Chloride, USP is chemically designated KCl, a white granular powder freely soluble in water.

Magnesium Chloride, USP hexahydrate is chemically designated MgCl2 • 6H2O, deliquescent crystals very soluble in water.

Sodium Acetate, USP anhydrous is chemically designated C2H3NaO2, a hygroscopic powder very soluble in water.

Water for Injection, USP is chemically designated H2O.

The semi-rigid container is fabricated from a specially formulated polyolefin. It is a copolymer of ethylene and propylene. The safety of the plastic has been confirmed by tests in animals according to USP biological standards for plastic containers. The container requires no vapor barrier to maintain the proper drug concentration.

CLINICAL PHARMACOLOGY

TPN Electrolytes (multiple electrolyte additive) helps to maintain normal cellular metabolism during TPN (total parenteral nutrition). Providing electrolytes in appropriate amounts prevents deficiency symptoms which otherwise would occur in their absence.

Cations: Sodium is the principal extracellular cation; it helps maintain motor nerve depolarization, proper fluid balance and normal renal metabolism. Potassium is the principal intracellular cation; it helps transport dextrose across the cell membrane and contributes to normal renal function. Magnesium is an important cofactor for enzymatic reactions and helps to maintain normal CNS (central nervous system) activity and amino acid utilization. Calcium participates in muscle contraction, blood coagulation and helps maintain normal neuromuscular function.

Anions: Chloride is the principal extracellular anion which, along with bicarbonate, is involved in maintaining proper anion balance. Acetate is an important metabolic intermediate in the tricarboxylic acid cycle and is a bicarbonate alternate.

The distribution and excretion of sodium (Na^+) and chloride (Cl^−) are largely under the control of the kidney which maintains a balance between intake and output.

Approximately 80% of body calcium (Ca^++) is excreted in the feces as insoluble salts; urinary excretion accounts for the remaining 20%.

Potassium (K^+) is found in low concentration in the plasma and extracellular fluids (3.5 to 5.0 mEq/liter in a healthy adult). Normally about 80% to 90% of the potassium intake is excreted in the urine, the remainder in the stools and to a small extent, in the perspiration. The kidney does not conserve potassium well so that during fasting or in patients on a potassium-free diet, potassium loss from the body continues resulting in potassium depletion.

Magnesium (Mg^++) is the second most plentiful intracellular cation. Normal plasma concentration ranges from 1.5 to 2.5 or 3.0 mEq per liter. Magnesium is excreted solely by the kidney at a rate proportional to the plasma concentration and glomerular filtration.

Acetate (CH3COO^−) provides bicarbonate (HCO3^−) by metabolic conversion in the liver. This has been shown to proceed readily even in the presence of severe liver disease.

INDICATIONS AND USAGE

TPN Electrolytes (multiple electrolyte additive) is indicated for use as a supplement to nutritional solutions containing concentrated dextrose and amino acids delivered by central venous infusion, to help maintain electrolyte homeostasis in adult patients.

CONTRAINDICATIONS

TPN Electrolytes (multiple electrolyte additive) is contraindicated in pathological conditions where additives of potassium, sodium, calcium, magnesium or chloride could be clinically deleterious, e.g., anuria, hyperkalemia, heart block or myocardial damage and severe edema due to cardiovascular, renal or hepatic failure.

WARNINGS

CONCENTRATED, HYPERTONIC, ADDITIVE SOLUTION. Must be diluted in TPN solution prior to administration.

CONTAINS NO PHOSPHATE. Patients receiving TPN solutions containing concentrated dextrose require additive phosphate, in addition to TPN Electrolytes. Between 10 and 15 mM (310 to 465 mg) phosphorus are physically compatible with as much as 10 to 12 mEq calcium in the same admixture. The phosphate supplement should first be added to the amino acid or dextrose bottle and diluted well to avoid precipitation with calcium.

CONTAINS 20 mEq of POTASSIUM. The potassium content of other additives, such as potassium phosphate or potassium-containing antibiotics, must be considered in the context of total potassium delivered. TPN patients usually require 30 to 50 mEq of potassium per liter of TPN solution containing concentrated (20—25%) dextrose.

NOT INTENDED FOR PEDIATRIC USE.

Solutions containing sodium ions should be used with great care, if at all, in patients with congestive heart failure, severe renal insufficiency and in clinical states in which there exists edema with sodium retention.

Solutions which contain potassium ions should be used with great care, if at all, in patients with hyperkalemia, severe renal failure and in conditions in which potassium retention is present.

In patients with diminished renal function, administration of solutions containing sodium or potassium ions may result in sodium or potassium retention.

Solutions containing acetate ions should be used with great care in patients with metabolic or respiratory alkalosis. Acetate should be administered with great care in those conditions in which there is an increased level or an impaired utilization of this ion, such as severe hepatic insufficiency.

Warning: This product contains aluminum that may be toxic. Aluminum may reach toxic levels with prolonged parenteral administration if kidney function is impaired. Premature neonates are particularly at risk because their kidneys are immature, and they require large amounts of calcium and phosphate solutions, which contain aluminum.

Research indicates that patients with impaired kidney function, including premature neonates, who receive parenteral levels of aluminum at greater than 4 to 5 mcg/kg/day accumulate aluminum levels associated with central nervous system and bone toxicity. Tissue loading may occur at even lower rates of administration.

PRECAUTIONS

Do not administer unless solution is clear and seal is intact. Discard unused portion.

Blood levels of sodium, potassium, calcium, magnesium, phosphorus and chloride should be monitored frequently during TPN (total parenteral nutrition). Significant deviations from normal may justify further supplementation or substitution of individual electrolyte additives (in place of TPN Electrolytes) to tailor the electrolyte supplement to meet individual patient requirements.

In patients with renal dysfunction or cardiovascular insufficiency, especially in elderly or postsurgical patients, consider the potential effects of sodium (35 mEq) and potassium (20 mEq) present in TPN Electrolytes.

Extraordinary electrolyte losses are not necessarily corrected by TPN Electrolytes. In protracted vomiting or diarrhea or in patients with fistula drainage or nasogastric suction, separate replacement therapy may be necessary, based upon analysis of losses sustained.

Caution must be exercised in the administration of parenteral fluids, especially those containing sodium ions, to patients receiving corticosteroids or corticotropin.

Solutions containing acetate ions should be used with caution as excess administration may result in metabolic alkalosis.

Pregnancy

Animal reproduction studies have not been conducted with TPN Electrolytes. It is also not known whether TPN Electrolytes can cause fetal harm when administered to a pregnant woman or can affect reproduction capacity. TPN Electrolytes should be given to a pregnant woman only if clearly needed.

GERIATRIC USE

An evaluation of current literature revealed no clinical experience identifying differences in response between elderly and younger patients. In general, dose selection for an elderly patient should be cautious, usually starting at the low end of the dosing range, reflecting the greater frequency of decreased hepatic, renal, or cardiac function, and of concomitant disease or other drug therapy.

Sodium ions and phosphorus are known to be substantially secreted by the kidney, and the risk of toxic reactions may be greater in patients with impaired renal function. Because elderly patients are more likely to have decreased renal function, care should be taken in dose selection, and it may be useful to monitor renal function.

ADVERSE REACTIONS

Symptoms may result from an excess or deficit of one or more of the ions present in TPN Electrolytes. Therefore, frequent monitoring of electrolyte blood levels is recommended. Sodium excess can cause edema and exacerbation of congestive heart failure. Excess potassium can cause deviations from the normal ECG (electrocardiogram). Potassium deficits can impair neuromuscular function, causing muscle weakness or frank paralysis, intestinal dilatation and ileus. Calcium deficits can produce neuromuscular hyperexcitability, ranging from paresthesias, cramps and laryngospasm to tetany and grand mal seizures. Depressed calcium levels can accompany administration of parenteral phosphorous or large amounts of albumin. Magnesium deficiency can precipitate neuromuscular dysfunction, hyperirritability, psychotic behavior, tachycardia and hypertension. Magnesium excess can cause muscle weakness, ECG changes, sedation and mental confusion.

DRUG ABUSE AND DEPENDENCE

None known.

OVERDOSAGE

In the event of overhydration or solute overload, re-evaluate the patient and institute appropriate corrective measures. See WARNINGS and PRECAUTIONS.

DOSAGE AND ADMINISTRATION

One 20 mL volume of TPN Electrolytes (multiple electrolyte additive) is added to each liter of amino acid/dextrose solution. Alternatively, the TPN Electrolytes can be added to the bottle of amino acids or concentrated dextrose, to permit addition of the necessary phosphate additive to the remaining bottle. This latter technique helps avoid physical incompatibilities between calcium and phosphorus. A potassium phosphate additive is recommended for addition to nutritional solutions containing TPN Electrolytes. Between 10 and 30 mEq of potassium (as phosphate) should be added per liter of TPN solution, to augment the 20 mEq of potassium provided by TPN Electrolytes.

Between two and three liters of TPN solution with added TPN Electrolytes are usually administered daily to adults. Solutions are given continuously over the entire 24-hour period at a constant rate, ranging from 83 to 125 mL/hour. TPN solutions containing TPN Electrolytes and concentrated dextrose are administered intravenously, through a central venous catheter.

Parenteral drug products should be inspected visually for particulate matter and discoloration prior to administration, whenever solution and container permit. See PRECAUTIONS.

HOW SUPPLIED

TPN Electrolytes (multiple electrolyte additive) is supplied in the following single-dose delivery system:

Unit of Sale | Concentration | Each
NDC 0409-5779-01 25 in a carton | 20 mL | NDC 0409-5779-11 20 mL Vial

Exposure of pharmaceutical products to heat should be minimized. Avoid excessive heat. Protect from freezing. Store at 20 to 25°C (68 to 77°F). [See USP Controlled Room Temperature.]

Distributed by Hospira, Inc., Lake Forest, IL 60045 USA

LAB-1091-1.0

Revised: 9/2017

PRINCIPAL DISPLAY PANEL - 20 mL Vial Label

20 mL Single-dose
TPN*
ELECTROLYTES

MULTIPLE ELECTROLYTE
ADDITIVE
Rx only

*Total Parenteral Nutrition

CAUTION: MUST BE DILUTED.
FOR INTRAVENOUS USE.

Distributed by Hospira, Inc., Lake Forest, IL 60045 USA

PRINCIPAL DISPLAY PANEL - 20 mL Vial Carton

20 mL Single-dose

NDC 0409-5779-01
Contains 25 of NDC 0409-5779-11

TPN* Electrolytes

Multiple Electrolyte Additive
*Total Parenteral Nutrition

Rx only

CAUTION: MUST BE DILUTED.
FOR INTRAVENOUS USE.

Hospira